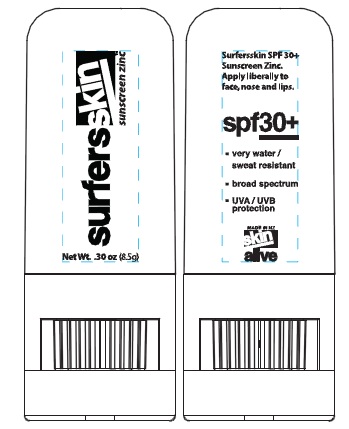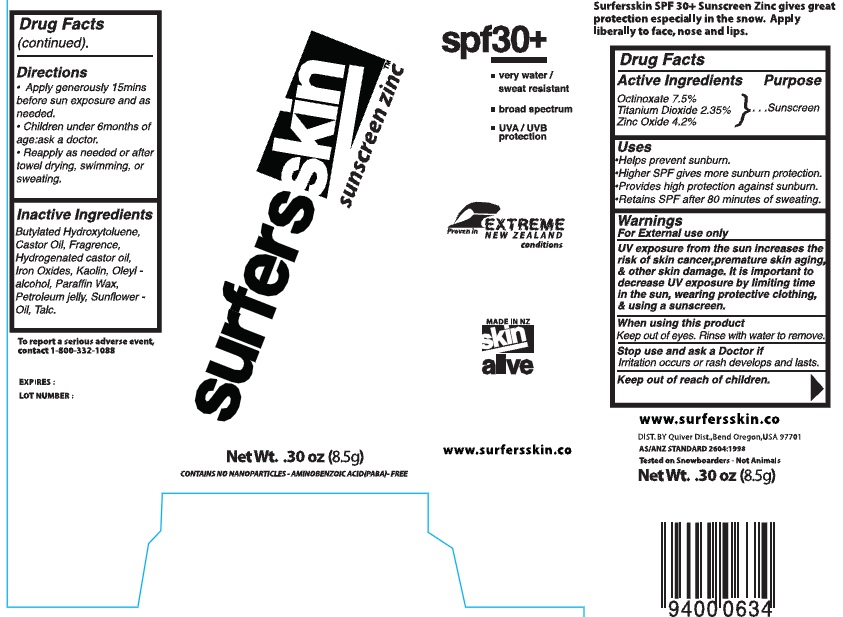 DRUG LABEL: SurfersSkin Sunscreen Zinc
NDC: 75916-0636 | Form: STICK
Manufacturer: Skin Alive, Ltd.
Category: otc | Type: HUMAN OTC DRUG LABEL
Date: 20110127

ACTIVE INGREDIENTS: OCTINOXATE 7.5 g/100 g; TITANIUM DIOXIDE 2.35 g/100 g; ZINC OXIDE 4.2 g/100 g
INACTIVE INGREDIENTS: BUTYLATED HYDROXYTOLUENE; CASTOR OIL; HYDROGENATED CASTOR OIL; IRON; KAOLIN; OLEYL ALCOHOL; PARAFFIN; PETROLATUM; SUNFLOWER OIL; TALC

SurfersSkin Sunscreen Zinc

Active Ingredients

Octinoxate 7.5%

Titanium Dioxide 2.35%

Zinc Oxide 4.2%

Purpose

Sunscreen

Uses

Helps prevent sunburn

Higher SPF gives more sunburn protection

Provides high protection against sunburn

Regains SPF after 80 minutes of sweating.

Warnings

For external use only

UV exposure from the sun increases the risk of skin cancer, premature skin aging and other skin damage. It is important to decrease UV exposure by limiting time in the sun, wearing protective clothing and using a sunscreen.

When using this product

Keep out of eyes. Rinse with water to remove.

Stop use and ask a doctor

if irritation occurs or rash develops and lasts.

Directions

apply generously 15mins before sun exposure and as needed

Children under 6 months of age: ask a doctor.

Reapply as needed or after towel drying, swimming or sweating.

Inactive Ingredients

Butylated Hydroxytoluene, Castor oil, Fragrance, Hydrogenated castor oil, Iron Oxides, Kaolin, Oleyl-alcohol, paraffin wax, petroleum jelly, sunflower oil, Talc

DESCRIPTION

SurfersSkin SPF 30+ Sunscreen Zinc gives great protection especially in the snow. Apply liberally to face, nose and lips.

To report a serious adverse event, contact 1-800-332-1088

Expires:

Lot Number:

ww.snowskin.co

DIST. BY Quiver Dist, Bend Oregon, USA 97701

Tested on Snowboarders - Not animals

AS/ANZ STANDARD 2604-1998

Net Wt. 0.30oz (8.5g)

PACKAGE LABEL

SPF 30+

very water / sweat resistant

broad spectrum

UVA/UVB protection

Proven in extreme new zealand conditions

SufersSkin sunscreen Zinc

hands free

Net Wt. 0.30oz (8.5g)

contains no nanoparticles-aminobenzoic acid (PABA) free